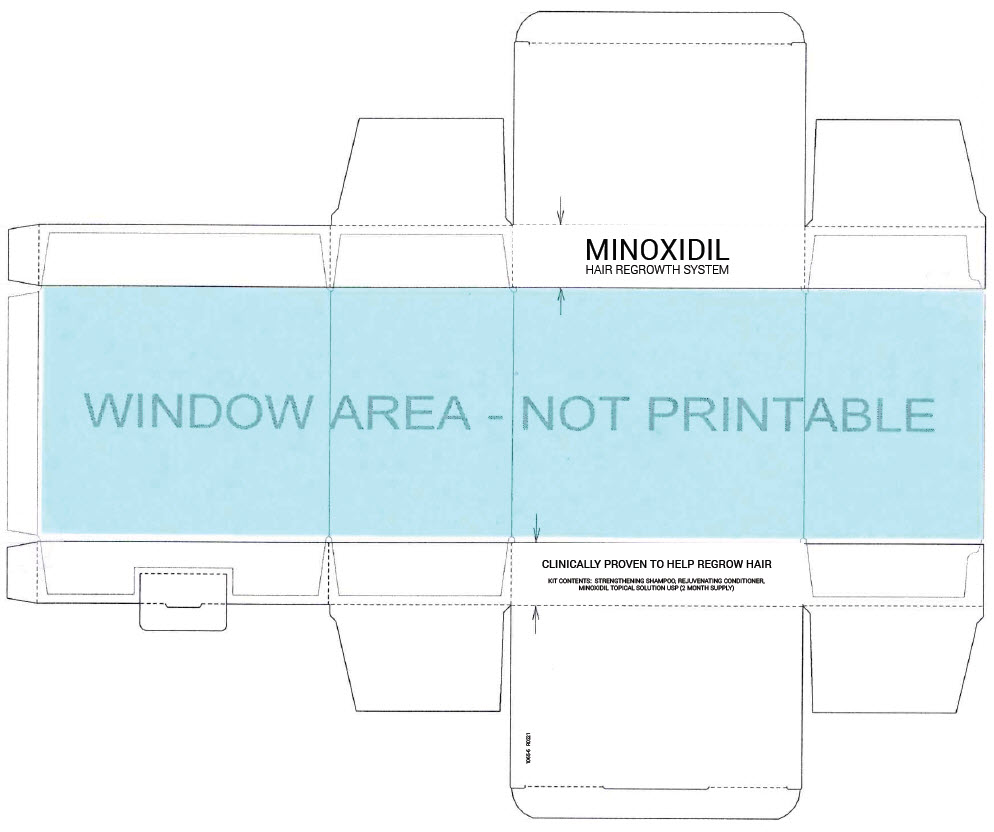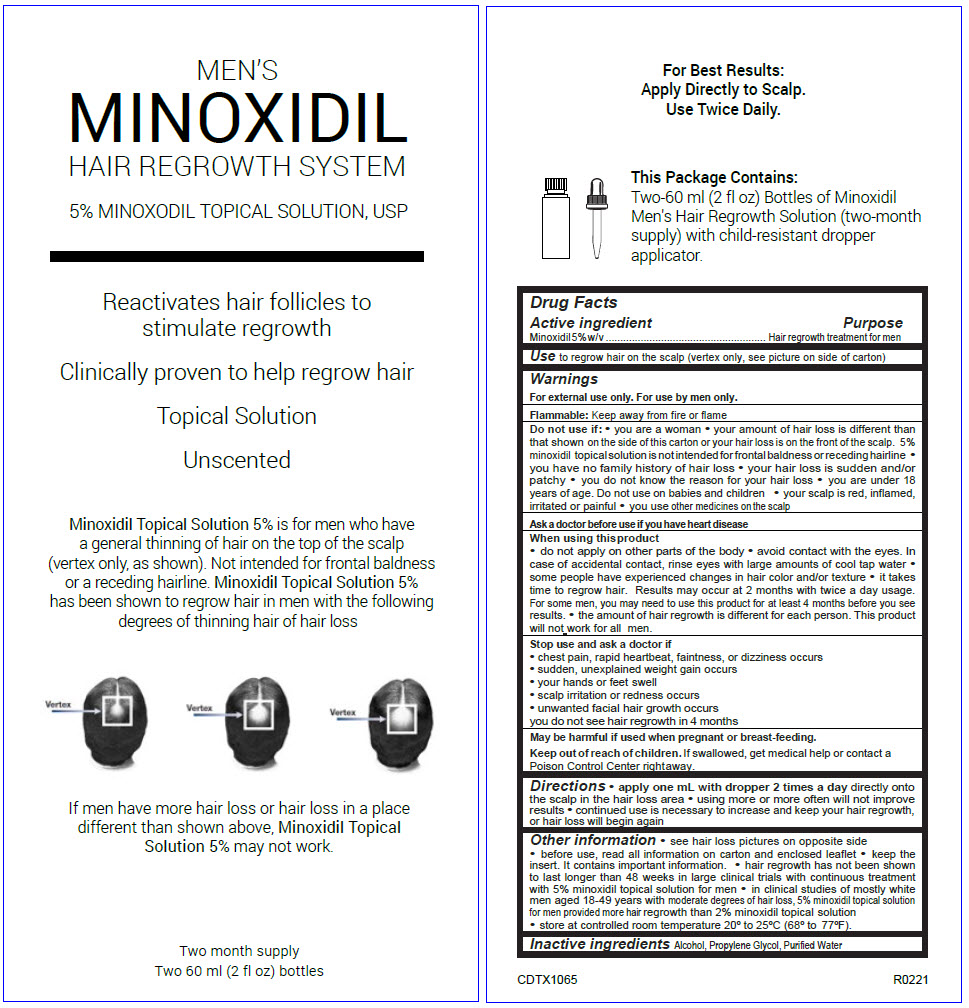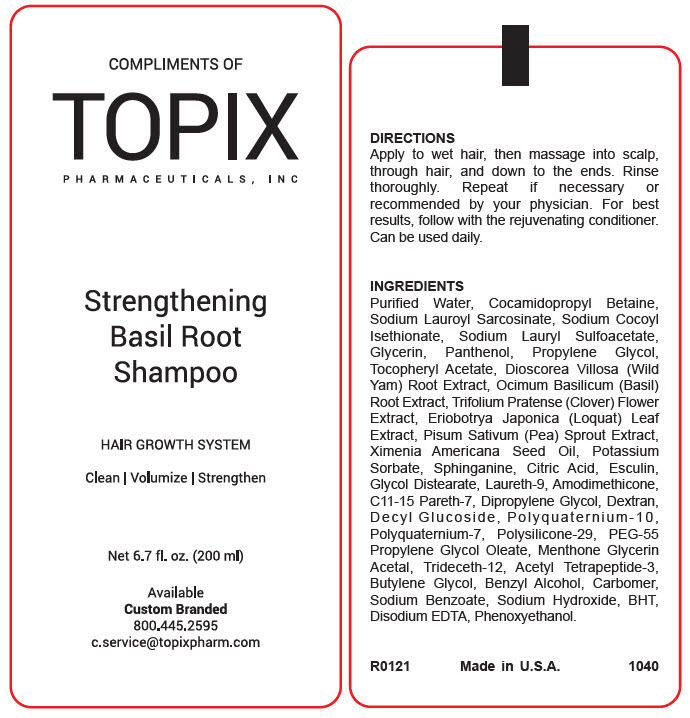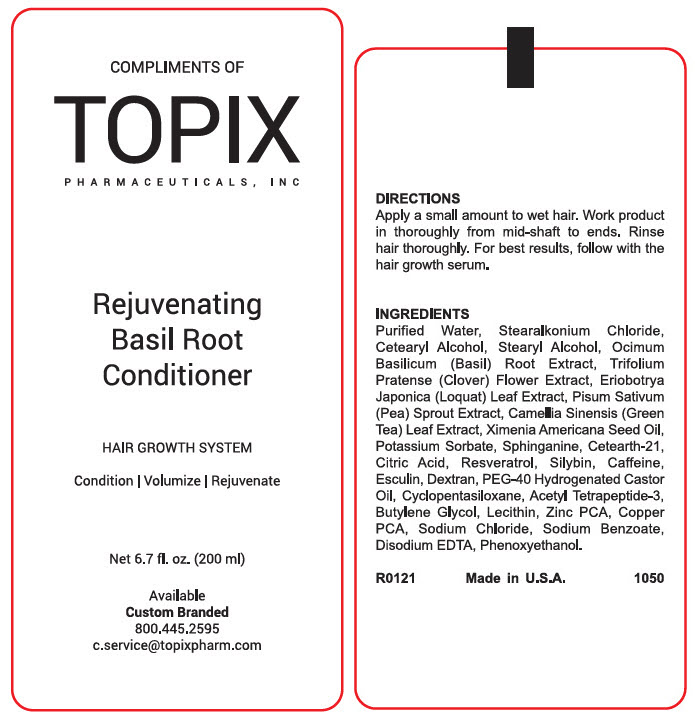 DRUG LABEL: Mens Minoxidil Hair Regrowth
NDC: 51326-165 | Form: KIT | Route: TOPICAL
Manufacturer: Topiderm, Inc
Category: otc | Type: HUMAN OTC DRUG LABEL
Date: 20241009

ACTIVE INGREDIENTS: MINOXIDIL 50 mg/1 mL
INACTIVE INGREDIENTS: ALCOHOL; PROPYLENE GLYCOL; WATER

Mens Minoxidil Hair Regrowth System

Drug Facts

Active ingredient

Minoxidil 5% w/v

Purpose

Hair regrowth treatment for men

Use

to regrow hair on the scalp (vertex only, see picture on side of carton)

Warnings

For external use only. For use by men only.

Flammable: Keep away from fire or flame

Do not use if

- you are a woman
- your amount of hair loss is different than that shown on the side of this carton or your hair loss is on the front of the scalp. 5% minoxidil topical solution is not intended for frontal baldness or receding hairline
- you have no family history of hair loss
- your hair loss is sudden and/or patchy
- you do not know the reason for your hair loss
- you are under 18 years of age. Do not use on babies and children
- your scalp is red, inflamed, irritated or painful
- you use other medicines on the scalp

Ask a doctor before use if you have heart disease

When using this product

- do not apply on other parts of the body
- avoid contact with the eyes. In case of accidental contact, rinse eyes with large amounts of cool tap water
- some people have experienced changes in hair color and/or texture
- it takes time to regrow hair. Results may occur at 2 months with twice a day usage. For some men, you may need to use this product for at least 4 months before you see results.
- the amount of hair regrowth is different for each person. This product will not work for all men.

Stop use and ask a doctor if

- chest pain, rapid heartbeat, faintness, or dizziness occurs
- sudden, unexplained weight gain occurs
- your hands or feet swell
- scalp irritation or redness occurs
- unwanted facial hair growth occurs

you do not see hair regrowth in 4 months

PREGNANCY OR BREAST FEEDING

May be harmful if used when pregnant or breast-feeding.

Keep out of reach of children. If swallowed, get medical help or contact a Poison Control Center right away.

Directions

- apply one mL with dropper 2 times a day directly onto the scalp in the hair loss area
- using more or more often will not improve results
- continued use is necessary to increase and keep your hair regrowth, or hair loss will begin again

Other information

- see hair loss pictures on opposite side
- before use, read all information on carton and enclosed leaflet
- keep the insert. It contains important information.
- hair regrowth has not been shown to last longer than 48 weeks in large clinical trials with continuous treatment with 5% minoxidil topical solution for men
- in clinical studies of mostly white men aged 18-49 years with moderate degrees of hair loss, 5% minoxidil topical solution for men provided more hair regrowth than 2% minoxidil topical solution
- store at controlled room temperature 20º to 25ºC (68º to 77ºF).

Inactive ingredients

Alcohol, Propylene Glycol, Purified Water

PRINCIPAL DISPLAY PANEL - Kit Carton

MINOXIDIL
HAIR REGROWTH SYSTEM

CLINICALLY PROVEN TO HELP REGROW HAIR

KIT CONTENTS: STRENGTHENING SHAMPOO, REJUVENATING CONDITIONER,
MINOXIDIL TOPICAL SOLUTION USP (2 MONTH SUPPLY)

PRINCIPAL DISPLAY PANEL - 2-60 ml Bottle Dropcard

MEN'S
MINOXIDIL
HAIR REGROWTH SYSTEM

5% MINOXODIL TOPICAL SOLUTION, USP

Reactivates hair follicles to
stimulate regrowth

Clinically proven to help regrow hair

Topical Solution

Unscented

Minoxidil Topical Solution 5% is for men who have
a general thinning of hair on the top of the scalp
(vertex only, as shown). Not intended for frontal baldness
or a receding hairline. Minoxidil Topical Solution 5%
has been shown to regrow hair in men with the following
degrees of thinning hair of hair loss

If men have more hair loss or hair loss in a place
different than shown above, Minoxidil Topical
Solution 5% may not work.

Two month supply
Two 60 ml (2 fl oz) bottles

PRINCIPAL DISPLAY PANEL - 200 ml Bottle Label-Shampoo

COMPLIMENTS OF
TOPIX
PHARMACEUTICALS, INC

Strengthening
Basil Root
Shampoo

HAIR GROWTH SYSTEM

Clean | Volumize | Strengthen

Net 6.7 fl. oz. (200 ml)

Available
Custom Branded
800.445.2595
c.service@topixpharm.com

PRINCIPAL DISPLAY PANEL - 200 ml Bottle Label-Conditioner

COMPLIMENTS OF
TOPIX
PHARMACEUTICALS, INC

Rejuvenating
Basil Root
Conditioner

HAIR GROWTH SYSTEM

Condition | Volumize | Rejuvenate

Net 6.7 fl. oz. (200 ml)

Available
Custom Branded
800.445.2595
c.service@topixpharm.com